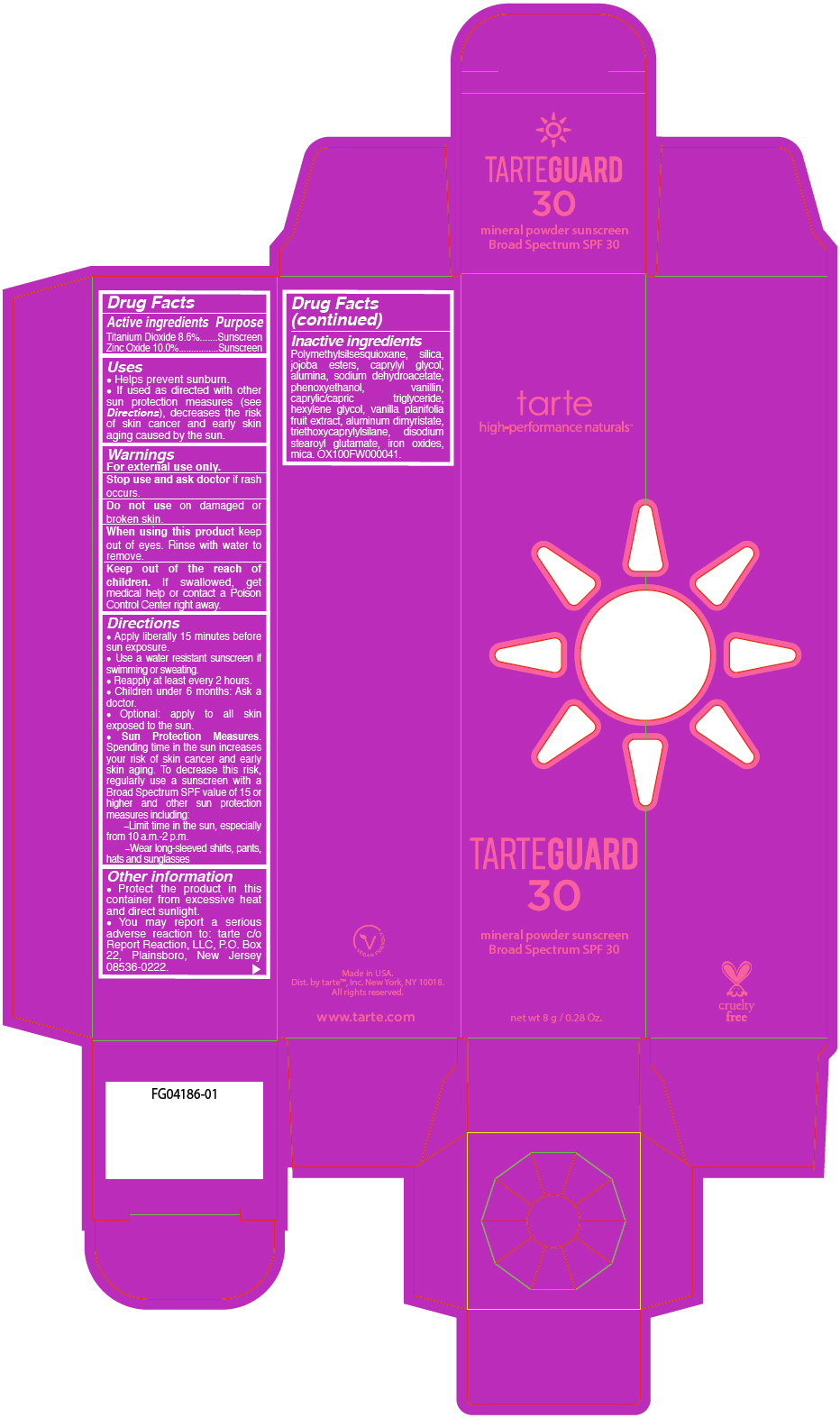 DRUG LABEL: Tarteguard Mineral Powder SPF 30
NDC: 51060-126 | Form: LIQUID
Manufacturer: Tarte, Inc
Category: otc | Type: HUMAN OTC DRUG LABEL
Date: 20180326

ACTIVE INGREDIENTS: Titanium Dioxide 86 mg/1 mL; Zinc Oxide 100 mg/1 mL
INACTIVE INGREDIENTS: POLYMETHYLSILSESQUIOXANE (4.5 MICRONS); SILICON DIOXIDE; CAPRYLYL GLYCOL; ALUMINUM OXIDE; SODIUM DEHYDROACETATE; PHENOXYETHANOL; VANILLIN; MEDIUM-CHAIN TRIGLYCERIDES; HEXYLENE GLYCOL; VANILLA; ALUMINUM DIMYRISTATE; TRIETHOXYCAPRYLYLSILANE; DISODIUM STEAROYL GLUTAMATE; FERRIC OXIDE RED

Tarteguard Mineral Powder SPF 30

Drug Facts

ACTIVE INGREDIENT

Active ingredients | Purpose
Titanium Dioxide 8.6% | Sunscreen
Zinc Oxide 10.0% | Sunscreen

Uses

- Helps prevent sunburn.
- If used as directed with other sun protection measures (see Directions), decreases the risk of skin cancer and early skin aging caused by the sun.

Warnings

For external use only.

Stop use and ask doctor if rash occurs.

Do not use on damaged or broken skin.

When using this product keep out of eyes. Rinse with water to remove.

KEEP OUT OF REACH OF CHILDREN

Keep out of the reach of children. If swallowed, get medical help or contact a Poison Control Center right away.

Directions

- Apply liberally 15 minutes before sun exposure.
- Use a water resistant sunscreen if swimming or sweating.
- Reapply at least every 2 hours.
- Children under 6 months: Ask a doctor.
- Optional: apply to all skin exposed to the sun.
- Sun Protection Measures. Spending time in the sun increases your risk of skin cancer and early skin aging. To decrease this risk, regularly use a sunscreen with a Broad Spectrum SPF value of 15 or higher and other sun protection measures including:
  –Limit time in the sun, especially from 10 a.m.-2 p.m.
  –Wear long-sleeved shirts, pants, hats and sunglasses

Other information

- Protect the product in this container from excessive heat and direct sunlight.
- You may report a serious adverse reaction to: tarte c/o Report Reaction, LLC, P.O. Box 22, Plainsboro, New Jersey 08536-0222.

Inactive ingredients

Polymethylsilsesquioxane, silica, jojoba esters, caprylyl glycol, alumina, sodium dehydroacetate, phenoxyethanol, vanillin, caprylic/capric triglyceride, hexylene glycol, vanilla planifolia fruit extract, aluminum dimyristate, triethoxycaprylylsilane, disodium stearoyl glutamate, iron oxides, mica. OX100FW000041.

Dist. by tarte™, Inc. New York, NY 10018.

PRINCIPAL DISPLAY PANEL - 8 g Tube Carton

tarte
high-performance naturals™

TARTEGUARD
30

mineral powder sunscreen
Broad Spectrum SPF 30

net wt 8 g / 0.28 Oz.